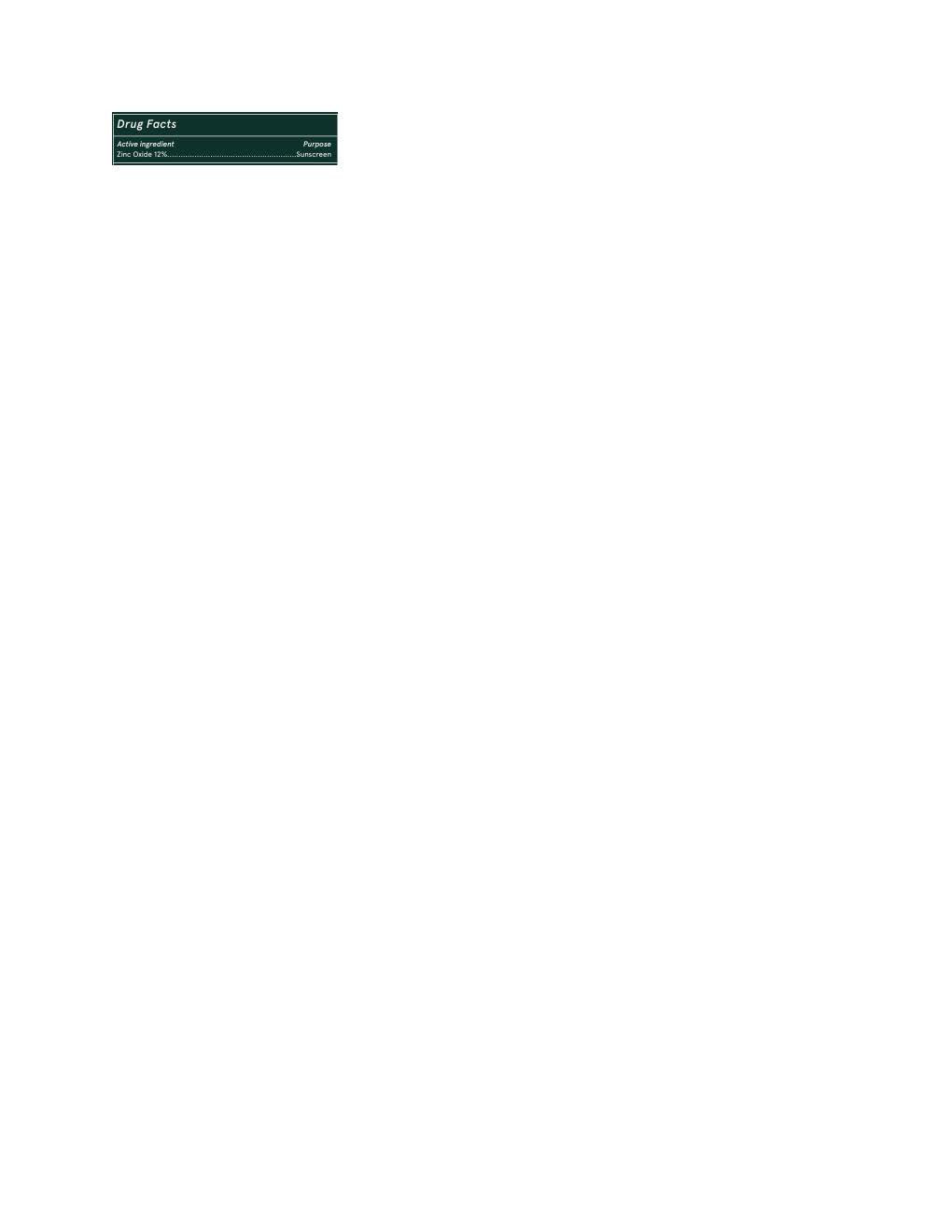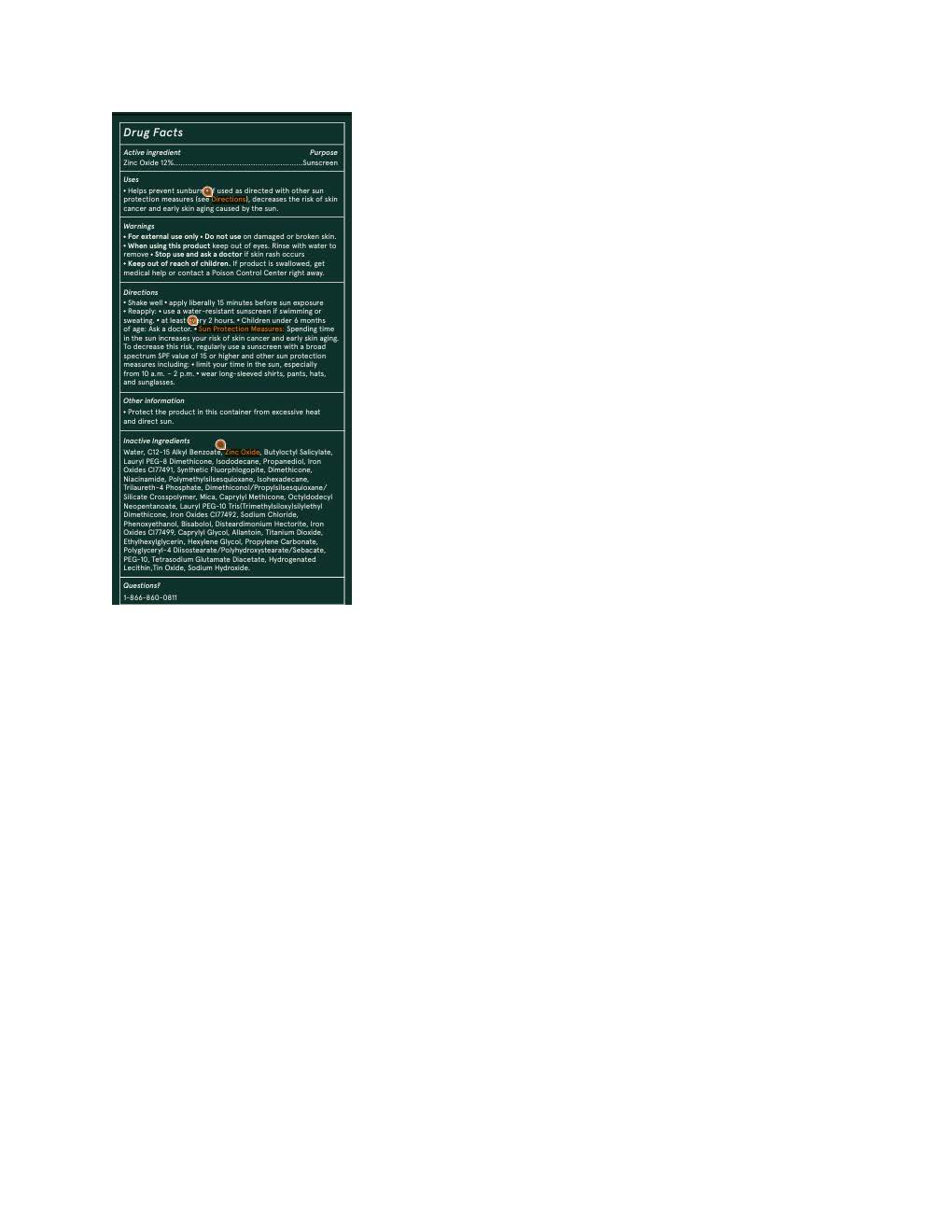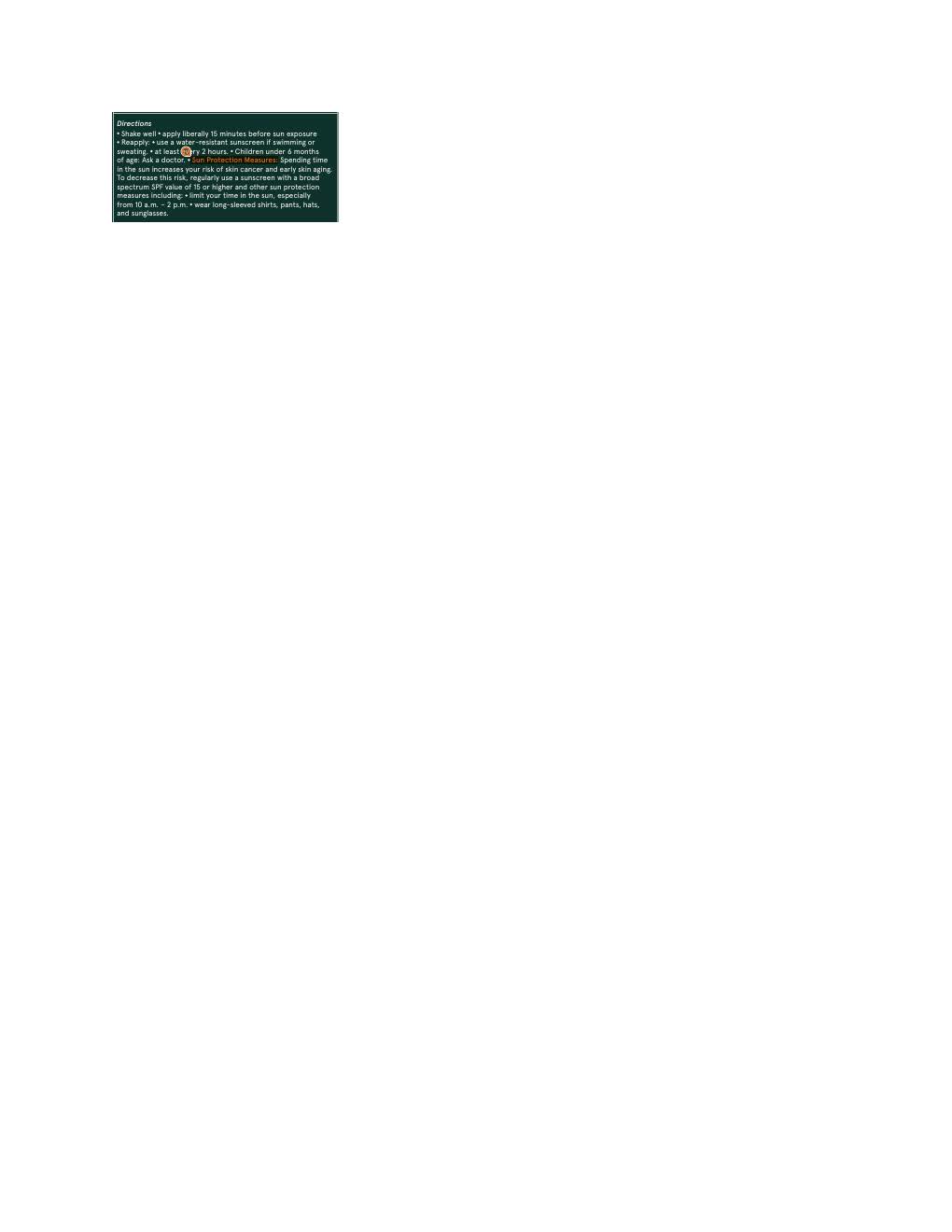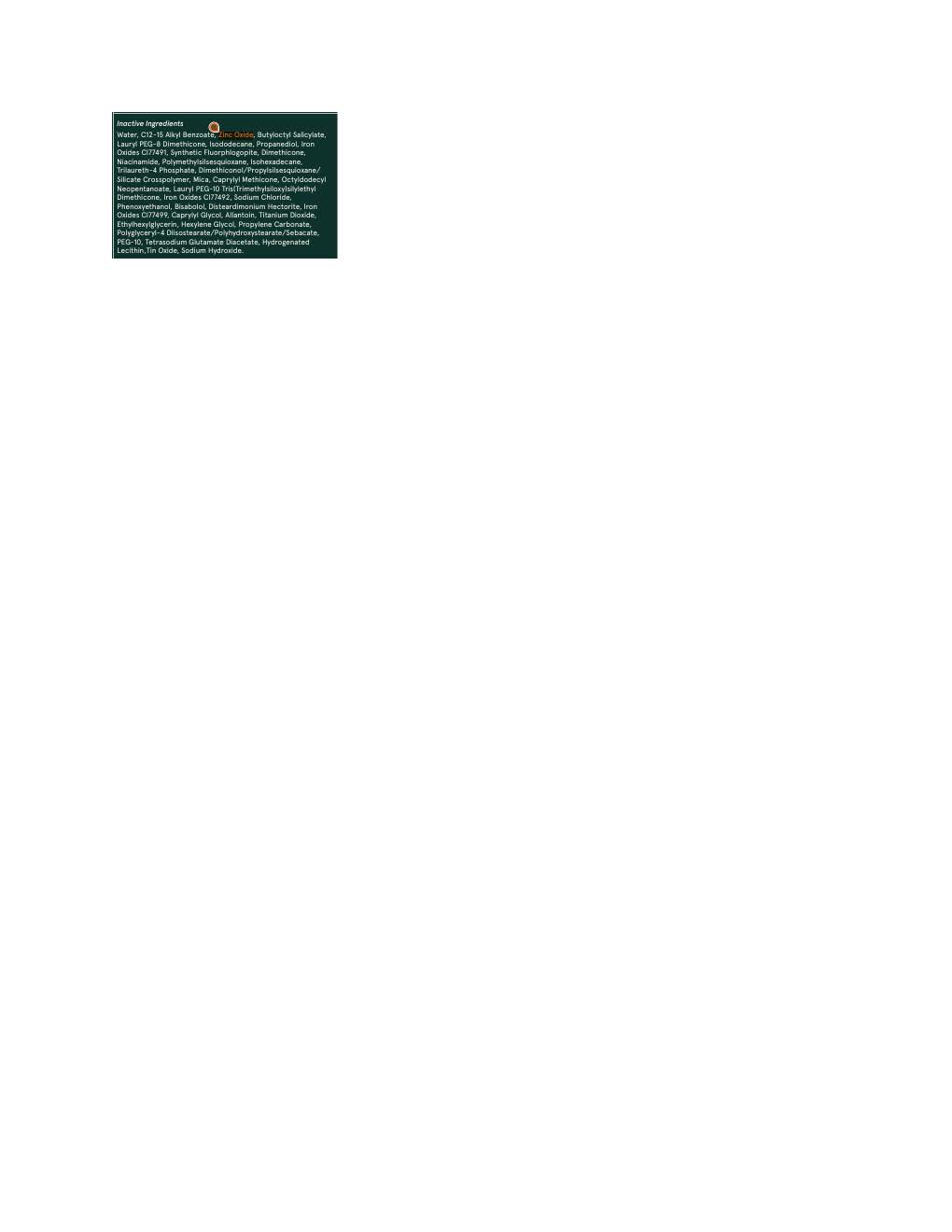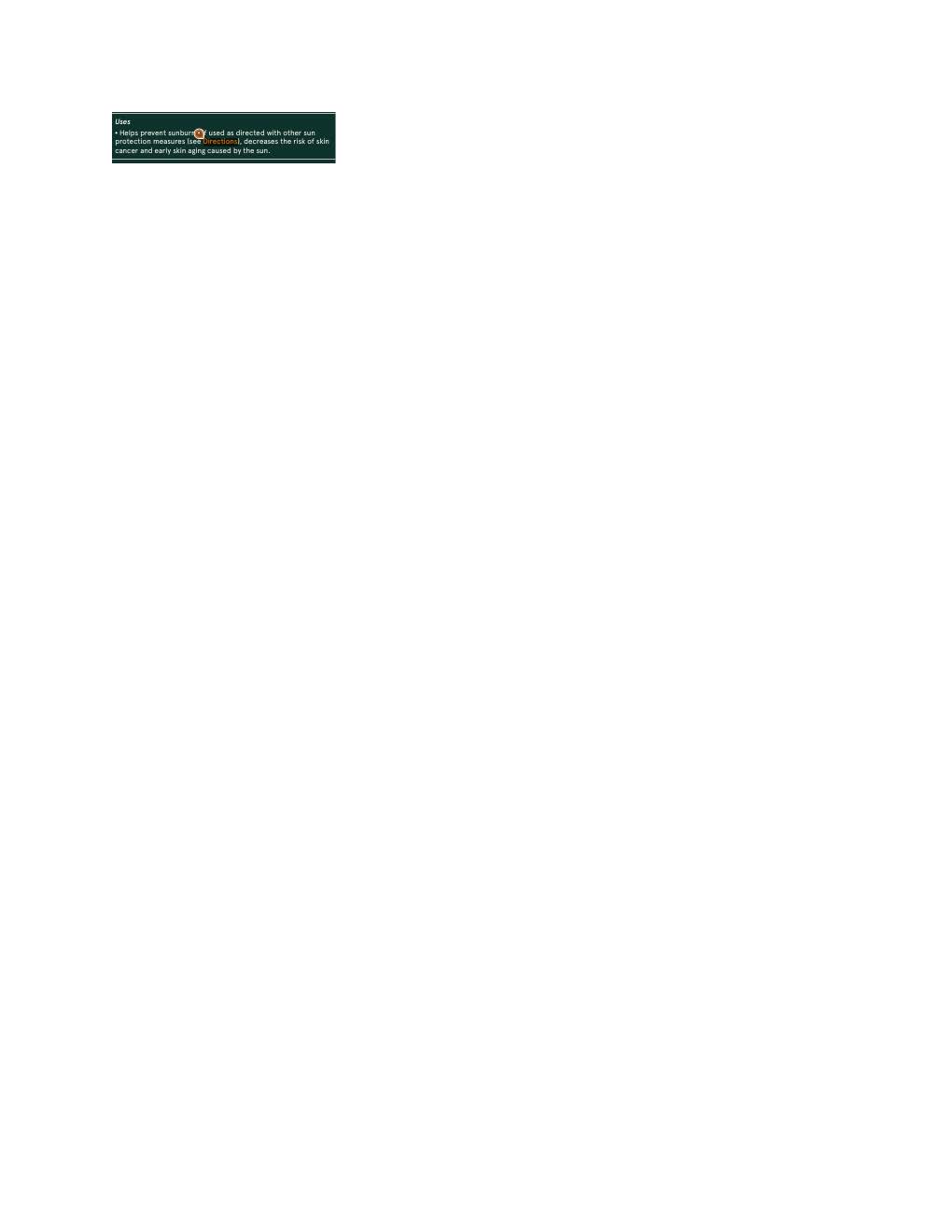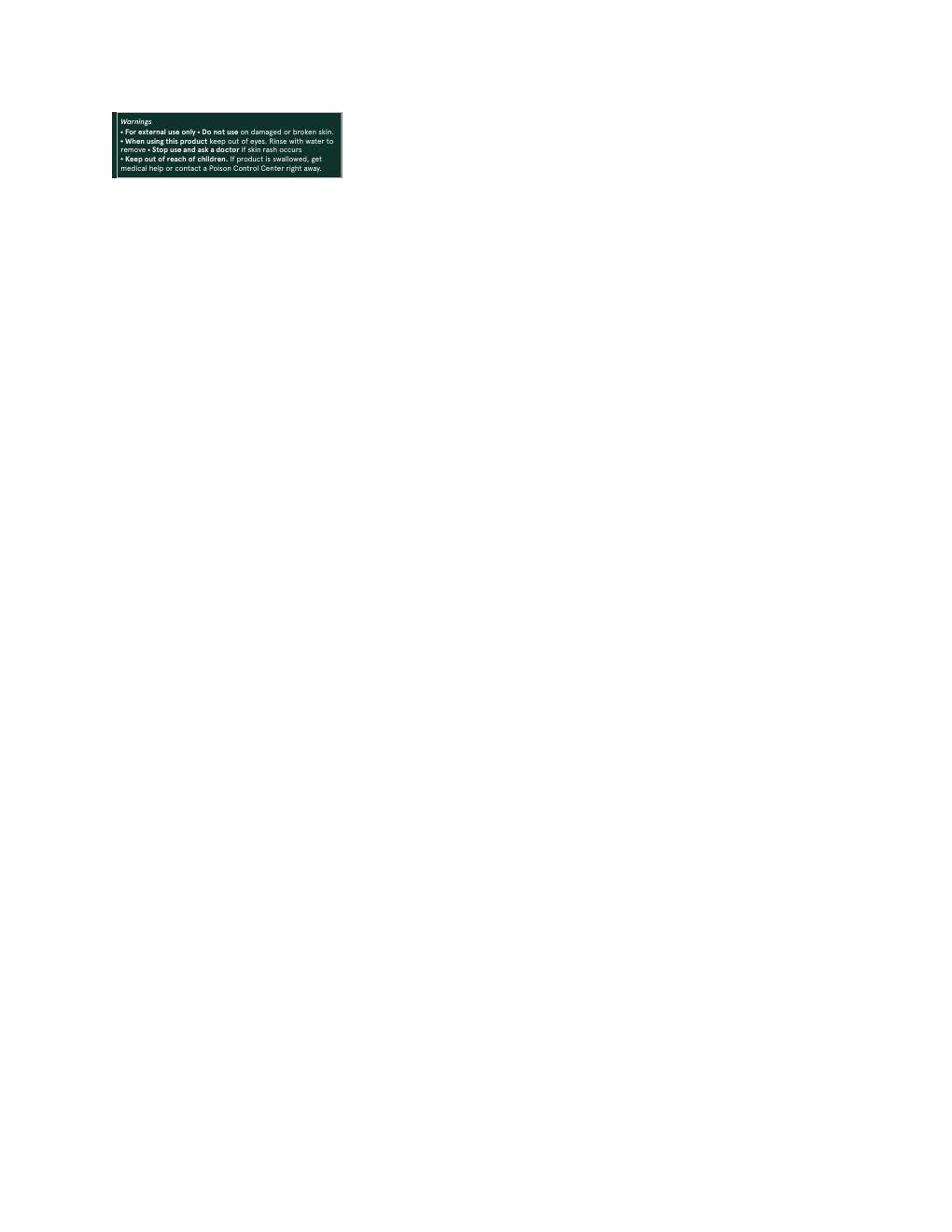 DRUG LABEL: Ciele Bronze and Protect
NDC: 83103-2255 | Form: LOTION
Manufacturer: Ciele LLC
Category: otc | Type: HUMAN OTC DRUG LABEL
Date: 20251015

ACTIVE INGREDIENTS: ZINC OXIDE 132 mg/1 mL
INACTIVE INGREDIENTS: MICA; LAURYL PEG-8 DIMETHICONE (300 CPS); FERRIC OXIDE YELLOW; ALKYL (C12-15) BENZOATE; POLYMETHYLSILSESQUIOXANE (4.5 MICRONS); DIMETHICONE; WATER; NIACINAMIDE; ETHYLHEXYLGLYCERIN; HEXYLENE GLYCOL; TRILAURETH-4 PHOSPHATE; DIMETHICONOL/PROPYLSILSESQUIOXANE/SILICATE CROSSPOLYMER (450000000 MW); PROPANEDIOL; TETRASODIUM GLUTAMATE DIACETATE; FERRIC OXIDE RED; SODIUM CHLORIDE; PHENOXYETHANOL; BUTYLOCTYL SALICYLATE; OCTYLDODECYL NEOPENTANOATE; ISODODECANE; .ALPHA.-BISABOLOL, (+)-; ALLANTOIN; CAPRYLYL GLYCOL; TITANIUM DIOXIDE; PROPYLENE CARBONATE; LECITHIN, SOYBEAN; DISTEARDIMONIUM HECTORITE; POLYGLYCERYL-4 DIISOSTEARATE/POLYHYDROXYSTEARATE/SEBACATE; ISOHEXADECANE; SODIUM HYDROXIDE

Ciele Bronze and Protect